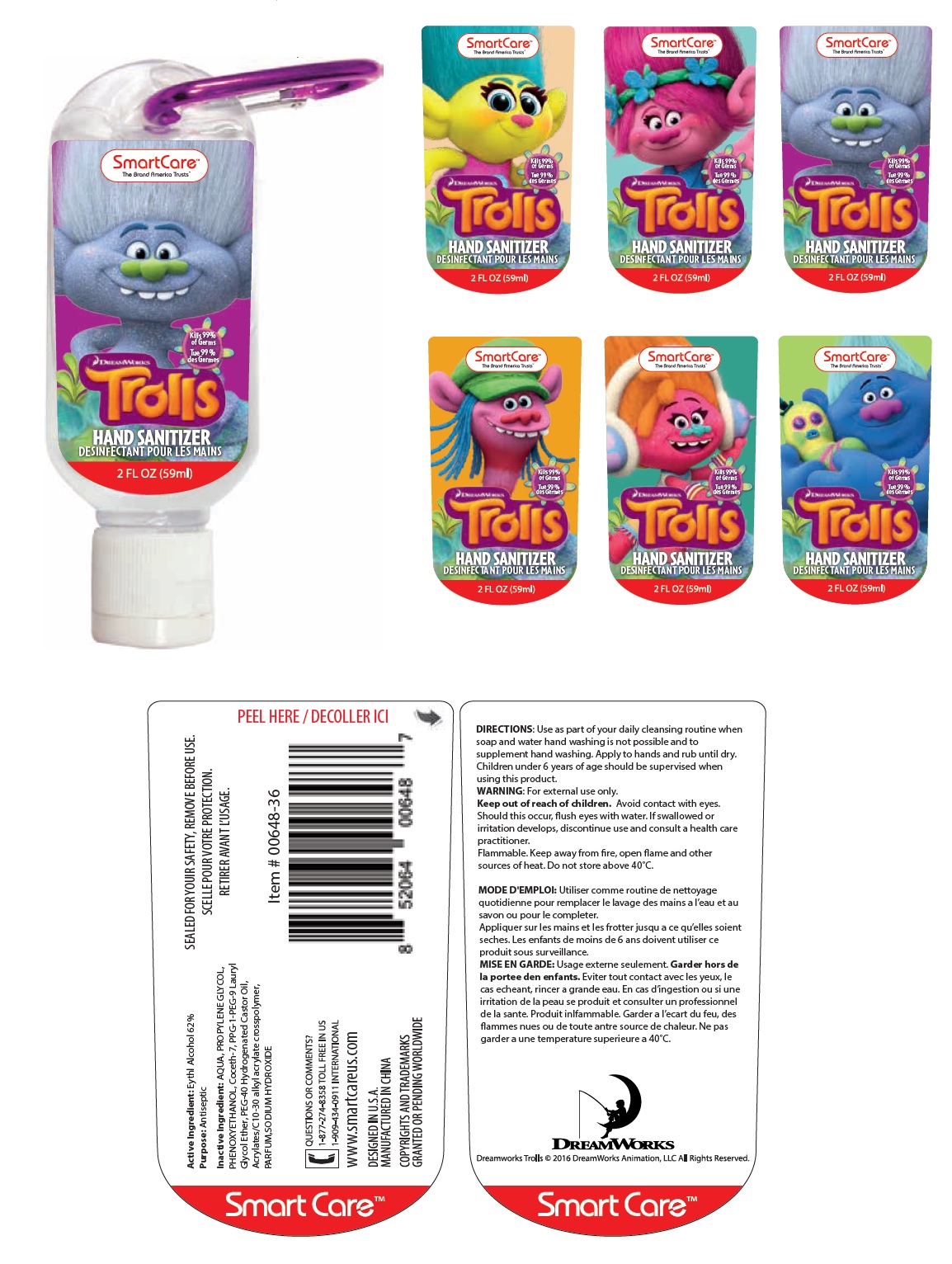 DRUG LABEL: Trolls Hand Sanitizer
NDC: 70108-032 | Form: GEL
Manufacturer: Ashtel Studios, Inc.
Category: otc | Type: HUMAN OTC DRUG LABEL
Date: 20200108

ACTIVE INGREDIENTS: ALCOHOL 62 g/100 mL
INACTIVE INGREDIENTS: WATER; PROPYLENE GLYCOL; PHENOXYETHANOL; COCETH-7; PPG-1-PEG-9 LAURYL GLYCOL ETHER; POLYOXYL 40 HYDROGENATED CASTOR OIL; CARBOMER INTERPOLYMER TYPE A (ALLYL SUCROSE CROSSLINKED); SODIUM HYDROXIDE

Trolls Hand Sanitizer

Active Ingredient:

Ethyl Alcohol 62%

Purpose:

Antiseptic

INDICATIONS AND USAGE

Use as part of your daily cleansing routine when soap and water hand washing is not possible and to supplement hand washing.

WARNINGS

WARNING: For external use only.
Flammable. Keep away from fire, open flame and other sources of heat. Do not store above 40°C.

Keep out of reach of children. Avoid contact with eyes.
Should this occur, flush eyes with water. If swallowed or irritation develops, discontinue use and consult a health care practitioner.

DOSAGE AND ADMINISTRATION

DIRECTIONS: Apply to hands and rub until dry. Children under 6 years of age should be supervised when using this product.

Inactive Ingredient: AQUA, PROPYLENE GLYCOL, PHENOXYETHANOL, Coceth-7, PPG-1-PEG-9 Lauryl Glycol Ether, PEG-40 Hydrogenated Castor Oil, Acrylates/C10-30 alkyl acrylate crosspolymer, PARFUM, SODIUM HYDROXIDE

QUESTIONS OR COMMENTS

1-877-274-8358 TOLL FREE IN US

1-909-434-0911 INTERNATIONAL

Kills 99% of Germs

SEALED FOR YOUR SAFETY, REMOVE BEFORE USE.

www.smartcareus.com

DESIGNED IN U.S.A

MANUFACTURED IN CHINA